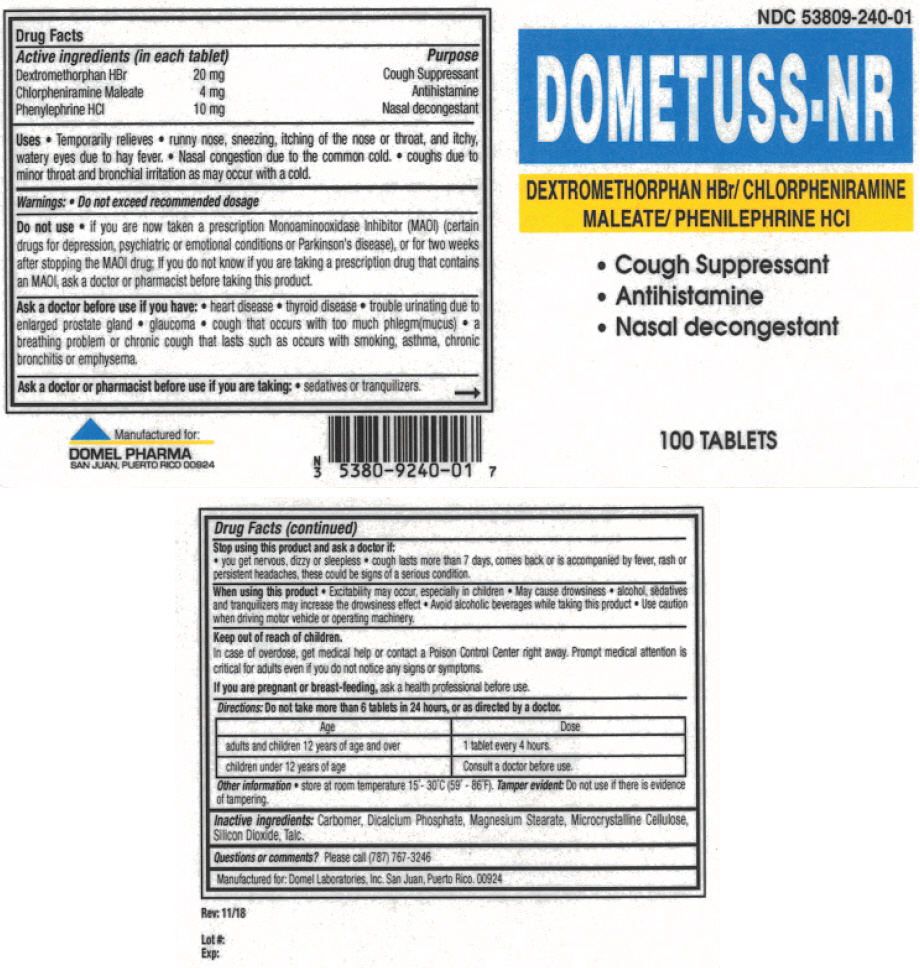 DRUG LABEL: DOMETUSS-NR
NDC: 53809-240 | Form: TABLET
Manufacturer: Domel Laboratories
Category: otc | Type: HUMAN OTC DRUG LABEL
Date: 20241206

ACTIVE INGREDIENTS: DEXTROMETHORPHAN HYDROBROMIDE 20 mg/1 1; CHLORPHENIRAMINE MALEATE 4 mg/1 1; PHENYLEPHRINE HYDROCHLORIDE 10 mg/1 1
INACTIVE INGREDIENTS: CARBOMER HOMOPOLYMER, UNSPECIFIED TYPE; ANHYDROUS DIBASIC CALCIUM PHOSPHATE; MAGNESIUM STEARATE; MICROCRYSTALLINE CELLULOSE; SILICON DIOXIDE; TALC

DOMETUSS-NR

Drug Facts

ACTIVE INGREDIENT

Active ingredients (in each tablet) |  | Purpose
Dextromethorphan HBr | 20 mg | Cough Suppressant
Chlorpheniramine Maleate | 4 mg | Antihistamine
Phenylephrine HCl | 10 mg | Nasal decongestant

Uses

- Temporarily relieves
  - runny nose, sneezing, itching of the nose or throat, and itchy, watery eyes due to hay fever.
  - Nasal congestion due to the common cold.
  - coughs due to minor throat and bronchial irritation as may occur with a cold.

Warnings

- Do not exceed recommended dosage

Do not use

- if you are now taken a prescription Monoaminooxidase Inhibitor (MAOI) (certain drugs for depression, psychiatric or emotional conditions or Parkinson's disease), or for two weeks after stopping the MAOI drug; If you do not know if you are taking a prescription drug that contains an MAOI, ask a doctor or pharmacist before taking this product.

Ask a doctor before use if you have

- heart disease
- thyroid disease
- trouble urinating due to enlarged prostate gland
- glaucoma
- cough that occurs with too much phlegm(mucus)
- a breathing problem or chronic cough that lasts such as occurs with smoking, asthma, chronic bronchitis or emphysema.

Ask a doctor or pharmacist before use if you are taking

- sedatives or tranquilizers.

Stop using this product and ask a doctor if

- you get nervous, dizzy or sleepless
- cough lasts more than 7 days, comes back or is accompanied by fever, rash or persistent headaches, these could be signs of a serious condition.

When using this product

- Excitability may occur, especially in children
- May cause drowsiness
- alcohol, sedatives and tranquilizers may increase the drowsiness effect
- Avoid alcoholic beverages while taking this product
- Use caution when driving motor vehicle or operating machinery.

Keep out of reach of children.

In case of overdose, get medical help or contact a Poison Control Center right away. Prompt medical attention is critical for adults even if you do not notice signs or symptoms.

PREGNANCY OR BREAST FEEDING

If you are pregnant or breast-feeding, ask a health professional before use.

Directions

Do not take more than 6 tablets in 24 hours, or as directed by a doctor.

Age | Dose
adults and children 12 years of age and over | 1 tablet every 4 hours.
children under 12 years of age | Consult a doctor before use.

Other information

- store at room temperature 15°- 30°C (59° - 86°F). Tamper evident: Do not use if there is evidence of tampering.

Inactive ingredients

Carbomer, Dicalcium Phosphate, Magnesium Stearate, Microcrystalline Cellulose, Silicon Dioxide, Talc.

Questions or comments?

Please call (787) 767-3246

PRINCIPAL DISPLAY PANEL - 100 Tablet Bottle Label

NDC 53809-240-01

DOMETUSS-NR

DEXTROMETHORPHAN HBr/ CHLORPHENIRAMINE
MALEATE/ PHENILEPHRINE HCl

- Cough Suppressant
- Antihistamine
- Nasal decongestant

100 TABLETS